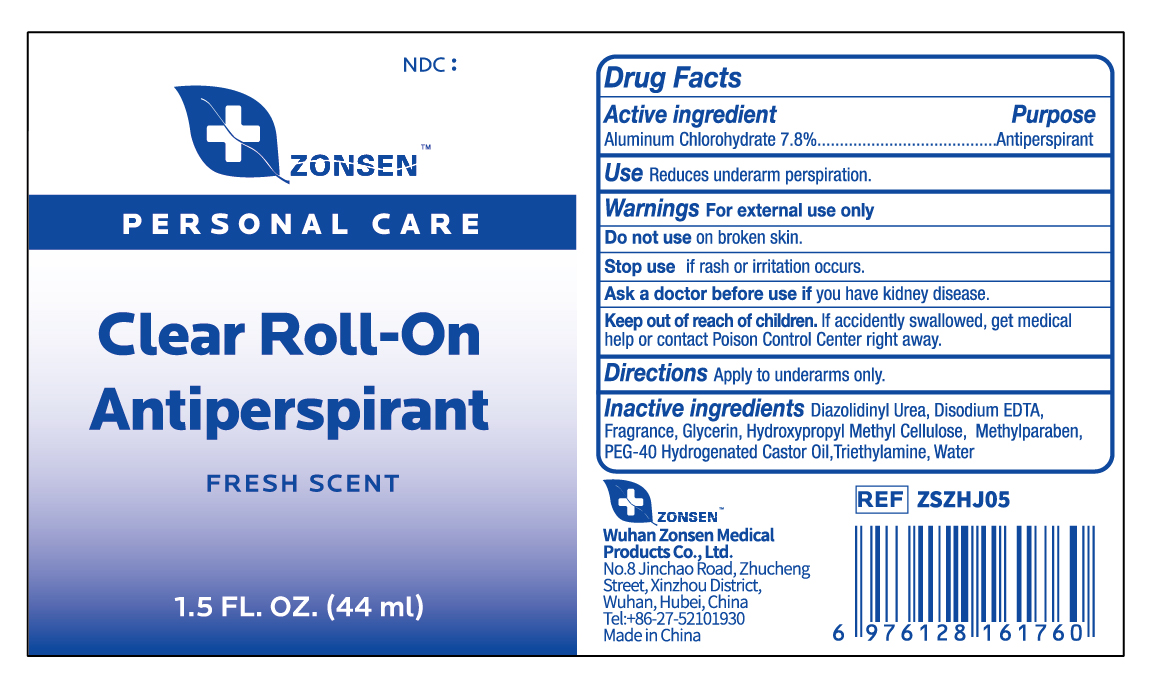 DRUG LABEL: ZONSEN Roll-On Antiperspirant
NDC: 72932-014 | Form: LOTION
Manufacturer: Wuhan Zonsen Medical Products Co., Ltd.
Category: otc | Type: HUMAN OTC DRUG LABEL
Date: 20240821

ACTIVE INGREDIENTS: ALUMINUM CHLOROHYDRATE 78 mg/1 mL
INACTIVE INGREDIENTS: POLYOXYL 40 HYDROGENATED CASTOR OIL; METHYLPARABEN; DIAZOLIDINYL UREA; HYPROMELLOSES; EDETATE DISODIUM; GLYCERIN; TRIETHYLAMINE; WATER

PURPOSE

Antiperspirant

Use

Reduces underarm perspiration.

ACTIVE INGREDIENT

Aluminum Chlorohydrate 7.8%

DO NOT USE

on broken skin.

DISCONTINUE USE IF

■irritation and redness develop

■ If condition persists for more than 72 hours consult a doctor.

Warnings

For external use only

Directions

Apply to underarms only.

ASK A DOCTOR BEFORE USE

if you have kidney disease.

KEEP OUT OF REACH OF CHILDREN

If swallowed, get medical help or contact Poison Control Center right away

INACTIVE INGREDIENT

Water, PEG-40 Hydrogenated Castor Oil, Diazolidinyl Urea, Hydroxyproply Methyl Cellulose, Glycerin, Methylparaben, Disodium EDTA,Triethylamine, Fragrance

DOSAGE & ADMINISTRATION

Use daily for best results.

BOTTLE LABEL

ZONSENTM

PERSONAL CARE

Clear Roll-On
Antiperspirant

FRESH SCENT

1.5 FL. OZ. (44ml)